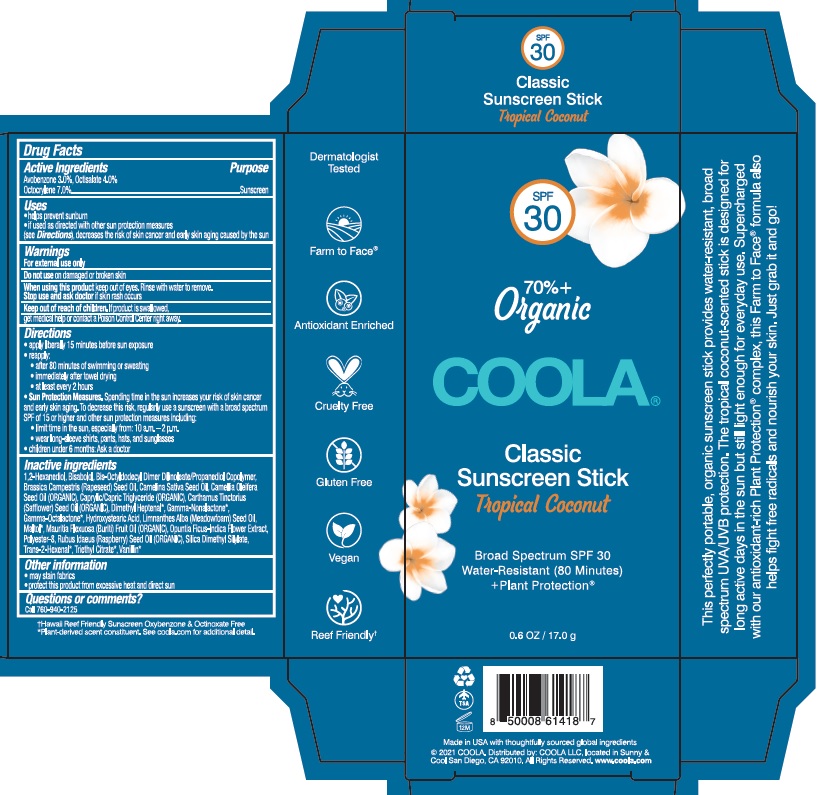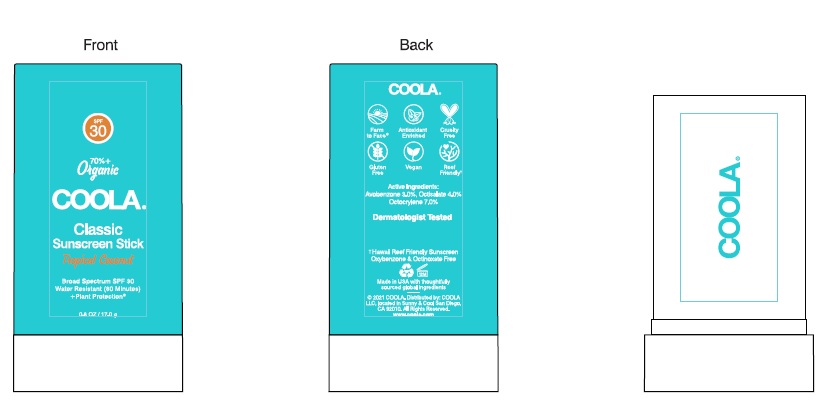 DRUG LABEL: COOLA Classic Sunscreen Stick SPF 30 - Tropical Coconut
NDC: 79753-016 | Form: STICK
Manufacturer: COOLA LLC
Category: otc | Type: HUMAN OTC DRUG LABEL
Date: 20210106

ACTIVE INGREDIENTS: AVOBENZONE 3.0 g/100 g; OCTISALATE 4.0 g/100 g; OCTOCRYLENE 7.0 g/100 g
INACTIVE INGREDIENTS: 1,2-HEXANEDIOL; LEVOMENOL; BIS-OCTYLDODECYL DIMER DILINOLEATE/PROPANEDIOL COPOLYMER; BRASSICA RAPA SUBSP. OLEIFERA OIL; CAMELINA SATIVA SEED OIL; CAMELLIA OIL; MEDIUM-CHAIN TRIGLYCERIDES; SAFFLOWER OIL; 2,6-DIMETHYL-5-HEPTENAL; .GAMMA.-NONALACTONE; .GAMMA.-OCTALACTONE; 10-HYDROXYSTEARIC ACID; MEADOWFOAM SEED OIL; MALTOL; MAURITIA FLEXUOSA FRUIT OIL; OPUNTIA FICUS-INDICA LEAF; POLYESTER-8 (1400 MW, CYANODIPHENYLPROPENOYL CAPPED); RASPBERRY SEED OIL; SILICA DIMETHYL SILYLATE; 2-HEXENAL, (2E)-; TRIETHYL CITRATE; VANILLIN

COOLA Classic Sunscreen Stick SPF 30 - Tropical Coconut

Drug Facts

Active Ingredients

Avobenzone 3.0%, Octisalate 4.0%, Octocrylene 7.0%

Purpose

Suncreen

Uses

- helps prevent sunburn

- if used as directed with other sun protection measures

(see Directions), decreases the risk of skin cancer and

early skin aging caused by the sun

Warnings

For external use only

Do not use on damaged or broken skin

When using this product keep out of eyes.

Rinse with water to remove.

Do not use on damaged or broken skin

Stop use and ask doctor if skin rash occurs

Keep out of reach of children. If product is swallowed, get

medical help or contact a Poison Control Center right away.

Directions
• apply liberally 15 minutes before sun exposure.
• reapply:
● after 80 minutes of swimming or sweating
● immediately after towel drying
● at least every 2 hours
Sun Protection Measures. Spending time in the sun increases your risk of skin cancer
and early skin aging. To decrease this risk, regularly use a sunscreen with a broad spection
SPF of 15 or higher and other sun protection measures including:
● limit time in the sun, especially from: 10 a.m. - 2 p.m.
● wear long-sleeve shirts, pants, hats, and sunglasses
●Children under 6 months: Ask a doctor

Inactive Ingredients
1,2-Hexanediol, Bisabolol, Bis-Octyldodecyl Dimer Dilinoleate/Propanediol Copolymer,
Brassica Campestris (Rapeseed) Seed Oil, Camelina Sativa Seed Oil, Camellia Oleifera
Seed Oil (ORGANIC), Caprylic/Capric Triglyceride (ORGANIC), Carthamus Tinctorius
(Safflower) Seed Oil (ORGANIC), Dimethyl Heptenal*, Gamma-Nonalactone*,
Gamma-Octalactone*, Hydroxystearic Acid, Limnanthes Alba (Meadowfoam) Seed Oil,
Maltol*, Mauritia Flexuosa (Buriti) Fruit Oil (ORGANIC), Opuntia Ficus-Indica Flower Extract,
Polyester-8, Rubus Idaeus (Raspberry) Seed Oil (ORGANIC), Silica Dimethyl Silylate,
Trans-2-Hexenal*, Triethyl Citrate*, VANILLIN* OR VANADIUM*???*

Other information

- may stain fabrics
- protect this product from excessive heat and direct sun

Questions or comments?
Call 760-940-2125

COOLA Label

SPF

30

70%+

Organic

COOLA®

Classic

Sunscreen Stick

Tropical Coconut

Broad Spectrum SPF 30

Water Resistant (80 Minutes)

+Plant Protection®

0.6 OZ / 17.0 g

©2021 COOLA. Distributed by: COOLA LLC, located in Sunny &

Cool San Diego, CA 92010. All Rights Reserved. www.coola.com

Hawaii Reef Friendly Sunscreen Oxybenzone & Octinoxate Free
*Plant-derived scent constituent. See coola.com for additional detail.

Carton

Canister

res